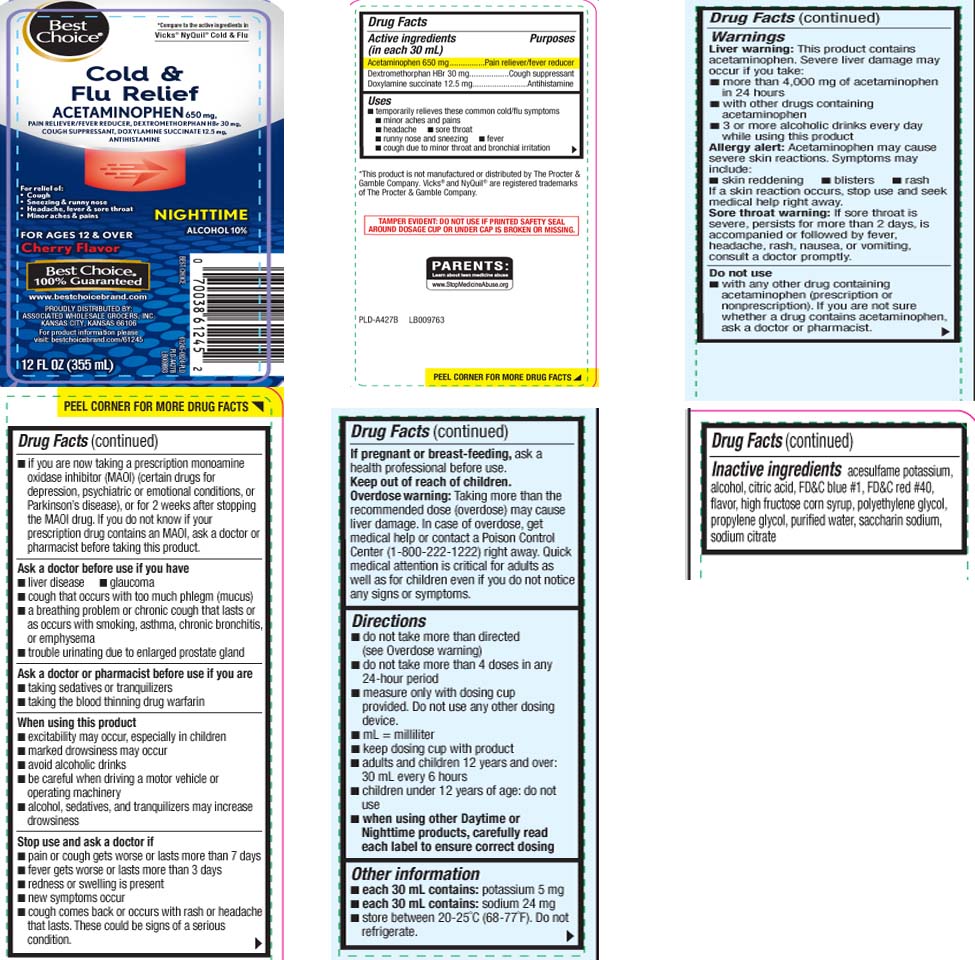 DRUG LABEL: Cold and Flu
NDC: 63941-343 | Form: LIQUID
Manufacturer: Best Choice  (Valu Merchandisers Company)
Category: otc | Type: HUMAN OTC DRUG LABEL
Date: 20260224

ACTIVE INGREDIENTS: ACETAMINOPHEN 650 mg/30 mL; DEXTROMETHORPHAN HYDROBROMIDE 30 mg/30 mL; DOXYLAMINE SUCCINATE 12.5 mg/30 mL
INACTIVE INGREDIENTS: PROPYLENE GLYCOL; WATER; ALCOHOL; ANHYDROUS CITRIC ACID; HIGH FRUCTOSE CORN SYRUP; POLYETHYLENE GLYCOL, UNSPECIFIED; SACCHARIN SODIUM; TRISODIUM CITRATE DIHYDRATE; FD&C BLUE NO. 1; FD&C RED NO. 40; ACESULFAME POTASSIUM

Drug Facts

Active ingredients (in each 30 mL)

Acetaminophen 650 mg

Dextromethorphan HBr 30 mg

Doxylamine succinate 12.5 mg

Purposes

Pain reliever/fever reducer

Cough suppressant

Antihistamine

Uses

temporarily relieves these common cold/flu symptoms:

- minor aches and pains
- headache
- sore throat
- fever
- runny nose and sneezing
- cough due to minor throat and bronchial irritation

Warnings

Liver warning: This product contains acetaminophen. Severe liver damage may occur if you take:

- more than 4,000 of acetaminophen in 24 hours
- with other drugs containing acetaminophen
- 3 or more alcoholic drinks every day while using this product

Allergy alert: Acetaminophen may cause severe skin reactions. Symptoms may include:

- skin reddening
- blisters
- rash

If a skin reaction occurs, stop use and seek medical help right away.

.Sore throat warning: If sore throat is severe, persists for more than 2 days, is accompanied or followed by fever, headache, rash, nausea, or vomiting, consult a doctor promptly.

Do not use

- if you are now taking a prescription monoamine oxidase inhibitor (MAOI) (certain drugs for depression, psychiatric or emotional conditions, or Parkinson’s disease), or for 2 weeks after stopping the MAOI drug. If you do not know if your prescription drug contains an MAOI, ask a doctor or pharmacist before taking this product.
- with any other drug containing acetaminophen (prescription or non-prescription). If you are not sure whether a drug contains acetaminophen, ask a doctor or pharmacist

Ask a doctor before use if you have

- liver disease
- glaucoma
- cough that occurs with too much phlegm (mucus)
- a breathing problem or chronic cough that lasts or as occurs with smoking, asthma, chronic bronchits, or emphysema
- trouble urinating due to enlarged prostate gland

Ask a doctor or pharmacist before use if you are taking

- sedatives or tranquilizers
- the blood thinning drug warfarin

When using this product

- excitability may occur, especially in children
- marked drowsiness may occur
- avoid alcoholic drinks
- be careful when driving a motor vehicle or operating machinery
- alcohol, sedatives and tranquilizers may increase drowsiness

Stop use and ask a doctor if

- pain or cough gets worse or lasts more than 7 days
- new symptoms occur
- fever gets worse or lasts more than 3 days
- redness or swelling is present
- cough comes back or occurs with rash or headache that lasts.

These could be signs of a serious condition.

If pregnant or breast-feeding,

ask a health professional before use.

Keep out of reach of children.

Overdose warning: Taking more than the recommended dose (overdose) may cause liver damage. In case of overdose, get medical help or contact a Poison Control Center (1-800-222-1222) right away. Quick medical attention is critical for adults as well as for children even if you do not notice any signs or symptoms.

Directions

- do not take more than directed (see Overdose warning)
- do not take more than 4 doses in any 24-hour period
- measure only with dosing cup provided. Do not use any other dosing device.
- mL= milliliter
- keep dosing cup with product
- adults and children 12 years and over: 30 mL every 6 hours
- children under 12 years of age: do not use
- When using other Day Time or Night Time products, carefully read each label to ensure correct dosing

Other information

- each 30 mL contains: potassium 5 mg
- each 30 mL contains: sodium 24 mg
- store between 20-25ºC (68-77ºF). Do not refrigerate

Inactive ingredients

acesulfame potassium, alcohol, citric acid, FD&C blue #1, FD&C red #40, flavor,high fructose corn syrup, polyethylene glycol, propylene glycol, purified water, saccharin sodium, sodium citrate

Questions or comments?

Call 1-877-753-3935 Monday-Friday 9AM-5PM EST

Principal Display Panel

*Compare to the active ingredients in Vicks® NyQuil® Cold & Flu

Cold & Flu Relief

ACETAMINOPHEN 650 mg, PAIN RELIEVER / FEVER REDUCER

DEXTROMETHORPHAN HBr 30 mg, COUGH SUPPRESSANT

DOXYLAMINE SUCCINATE 12.5 mg, ANTIHISTAMINE

For relief of:

- Cough
- Sneezing & runny nose
- Headache, fever & sore throat
- Minor aches & pains

FL OZ (mL)

FOR AGES 12 YEARS AND OVER

Cherry Flavor

NIGHTTIME

ALCOHOL 10%

*This product is not manufactured or distributed by The Procter & Gamble Company. Vicks® and NyQuil® are registered trademarks of the Procter & Gamble Company.

TAMPER EVIDENT: DO NOT USE IF PRINTED SAFETY SEAL AROUND DOSAGE CUP OR UNDER CAP IS BROKEN OR MISSING

PROUDLY DISTRIBUTED BY:

ASSOCIATED WHOLESALE GROCERS, INC.

KANSAS CITY, KANSAS 66106

Product Label

BEST CHOICE Nighttime Cold & Flu Relief Cherry Flavor